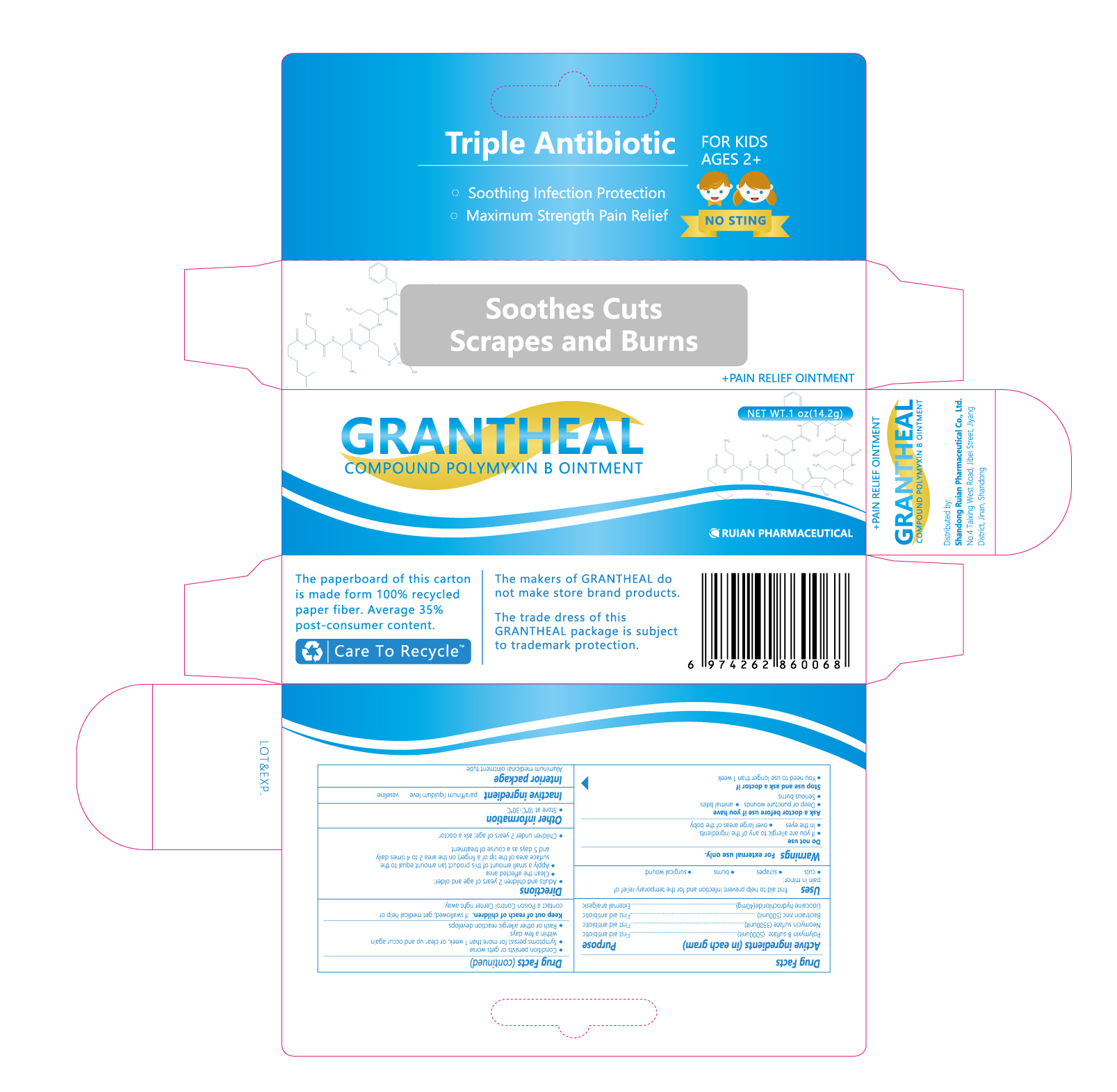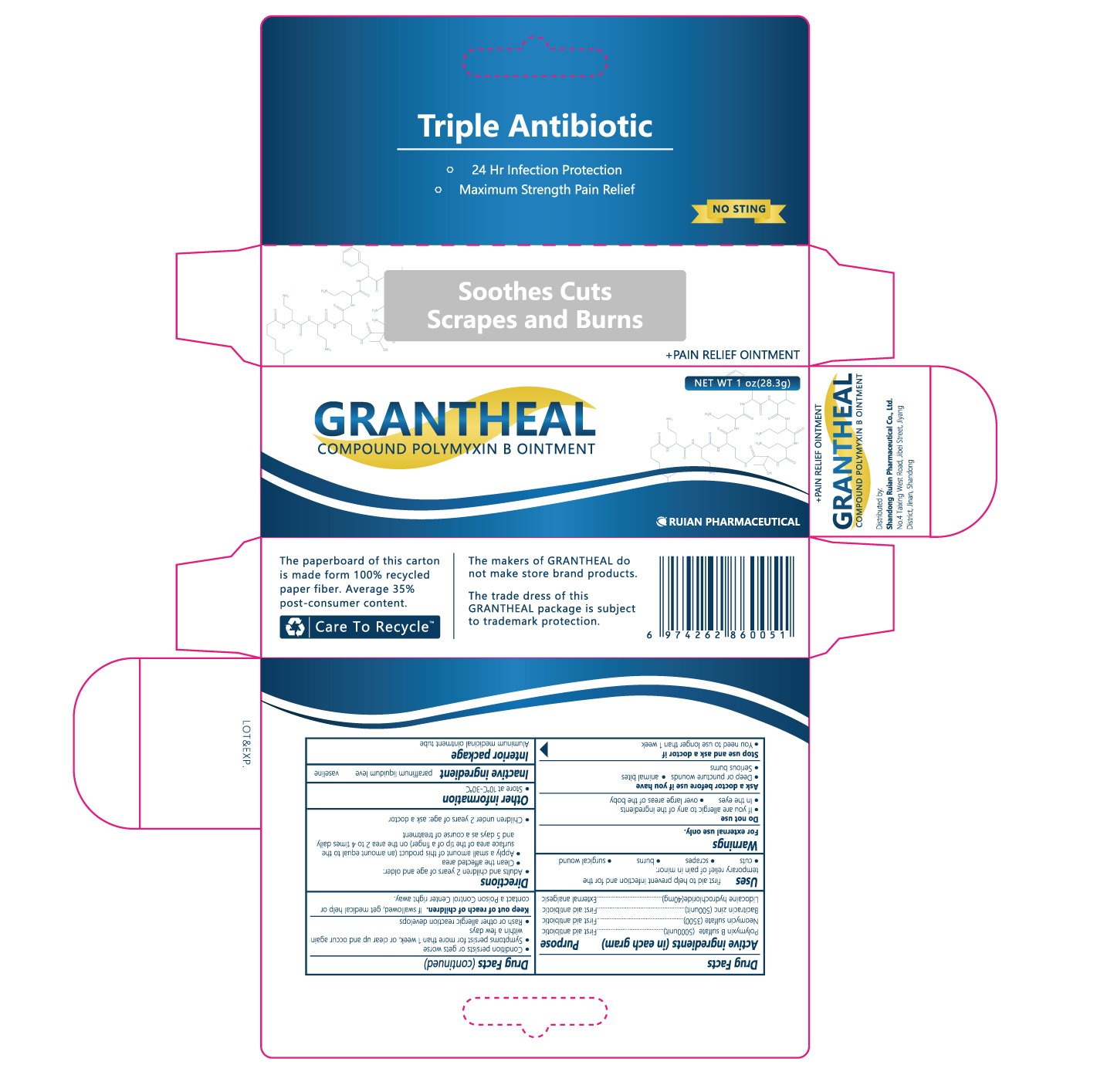 DRUG LABEL: Triple Antibiotic
NDC: 82199-531 | Form: OINTMENT
Manufacturer: Shandong Ruian Pharmaceutical Co.,Ltd.
Category: otc | Type: HUMAN OTC DRUG LABEL
Date: 20211118

ACTIVE INGREDIENTS: LIDOCAINE 40 mg/1 g; BACITRACIN ZINC 500 [USP'U]/1 g; NEOMYCIN SULFATE 3500 [USP'U]/1 g; POLYMYXIN B SULFATE 5000 [USP'U]/1 g
INACTIVE INGREDIENTS: PETROLATUM

ACTIVE INGREDIENT

POLYMYXIN B SULFATE;
NEOMYCIN SULFATE;
BACITRACIN ZINC;
LIDOCAINE HYDROCHLORIDE

PURPOSE

First aid antibiotic
External analgesic

INDICATIONS AND USAGE

first aid to help prevent infection and for the temporary relief of pain or discomfort in minor:
• cuts
• scrapes
• burns

WARNINGS

For external use only

DO NOT USE

• if you are allergic to any of the ingredients
• in the eyes
• over large areas of the body

ASK DOCTOR

• deep or puncture wounds
• animal bites
• serious burns

KEEP OUT OF REACH OF CHILDREN

If swallowed, get medical help or contact a Poison Control Center right away.

DOSAGE AND ADMINISTRATION

• adults and children 2 years of age or older:
• clean the affected area
• apply a small amount of this product (an amount equal to the surface area of the tip of a finger) on thearea 1 to 3 times daily
• may be covered with a sterile bandage
• children under 2 years of age: ask a doctor

OTHER SAFETY INFORMATION

store at 10°C-30°C

INACTIVE INGREDIENT

petrolatum

PACKAGE LABEL

NDC: 82199-531-13 14.2 g in 1 TUBE

NDC: 82199-531-14 28.3 g in 1 TUBE